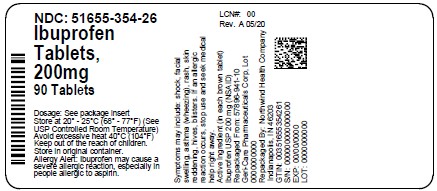 DRUG LABEL: Ibuprofen
NDC: 51655-354 | Form: TABLET, FILM COATED
Manufacturer: Northwind Health Company, LLC
Category: otc | Type: HUMAN OTC DRUG LABEL
Date: 20260101

ACTIVE INGREDIENTS: IBUPROFEN 200 mg/1 1
INACTIVE INGREDIENTS: CARNAUBA WAX; SILICON DIOXIDE; HYPROMELLOSES; LACTOSE; MAGNESIUM STEARATE; CELLULOSE, MICROCRYSTALLINE; POLYDEXTROSE; POLYETHYLENE GLYCOL, UNSPECIFIED; FERRIC OXIDE RED; STEARIC ACID; SODIUM STARCH GLYCOLATE TYPE A POTATO; TITANIUM DIOXIDE; STARCH, CORN

Active ingredient (in each brown tablet)

Ibuprofen USP, 200 mg (NSAID)*
*nonsteroidal anti-inflammatory drug

Purpose

Pain reliever/fever reducer

Uses

- Temporarily relieves minor aches and pains due to:
- headache
- toothache
- backache
- menstrual cramps
- the common cold
- muscular aches
- minor pain of arthritis

- Temporarily reduces fever

Warnings

Allergy Alert: Ibuprofen may cause a severe allergic reaction, especially in people allergic to aspirin. Symptoms may include:

- shock
- hives
- facial swelling
- asthma (wheezing)
- skin reddening
- rash
- blisters

If an allergic reaction occurs, stop use and seek medical help right away.
Stomach bleeding warning:

This product contains an NSAID, which may cause severe stomach bleeding. The chance is higher if you:

- are age 60 or older
- have had stomach ulcers or bleeding problems
- take a blood thinning (anticoagulant) or steroid drug
- take other drugs containing prescription or nonprescription NSAIDs (aspirin, ibuprofen, naproxen, or others)
- have 3 or more alcoholic drinks every day while using this product
- take more or for a longer time than directed
  Heart attack and stroke warning: NSAIDs, except aspirin, increase
  the risk of heart attack, heart failure, and stroke. These can be
  fatal. The risk is higher if you use more than directed or for
  longer than directed.

Do not use

- if you have ever had an allergic reaction to any other pain reliever/fever reducer
- right before or after heart surgery

Ask a doctor before use if

- the stomach bleeding warning applies to you
- you have problems or serious side effects from taking pain relievers or fever reducers
- you have a history of stomach problems, such as heartburn
- you have high blood pressure, heart disease, liver cirrhosis, kidney disease or asthma
- you are taking a diuretic

Ask a doctor or pharmacist before use if you are

- under a doctor’s care for any serious condition
- taking aspirin for heart attack or stroke, because ibuprofen may decrease this benefit of aspirin
- taking any other drug

When using this product

- take with food or milk if stomach upset occurs

Stop use and ask a doctor if

- you experience any of the following signs of stomach bleeding: -feel faint -vomit blood -have bloody or black stools -have stomach pain that does not get better
- you have symptoms of heart problems or stroke:
  - chest pain - trouble breathing - leg swelling
  - slurred speech - weakness in one part or side of body
- pain gets worse or lasts more than 10 days
- redness or swelling is present in the painful area
- fever gets worse or lasts more than 3 days
- any new symptoms occur

If pregnant or breast-feeding,

ask a health professional before use. it is especially important not to use ibuprofen during the last 3 months of pregnancy unless definitely directed to do so by a doctor because it may cause problems in the unborn child or complications during delivery.

Keep out of reach of children. In case of overdose , get medical help or contact a Poison Control Center (1-800-222-1222) right away.

Directions

- do not use more than directed
- the smallest effective dose should be used
- adults and children 12 years and over: take 1 tablet
  every 4 to 6 hours while symptoms persist
- if pain or fever does not respond to 1 tablet, 2 tablets
  may be used
- do not take more than 6 tablets in 24 hours unless directed by a doctor
- children under 12 years: ask a doctor

Other information

- store between 20°-25°C (68°-77°F)
- avoid excessive heat 40°C (104°F)

Inactive ingredients

carnauba wax, colloidal silicon dioxide, cellulose, corn starch, hypromellose, lactose, magnesium stearate, polydextrose, PEG, red iron oxide, sodium starch glycolate, stearic acid, titanium dioxide.

Questions or comments?

Call 1-800-540-3765

Package label

NDC: 51655-354-26